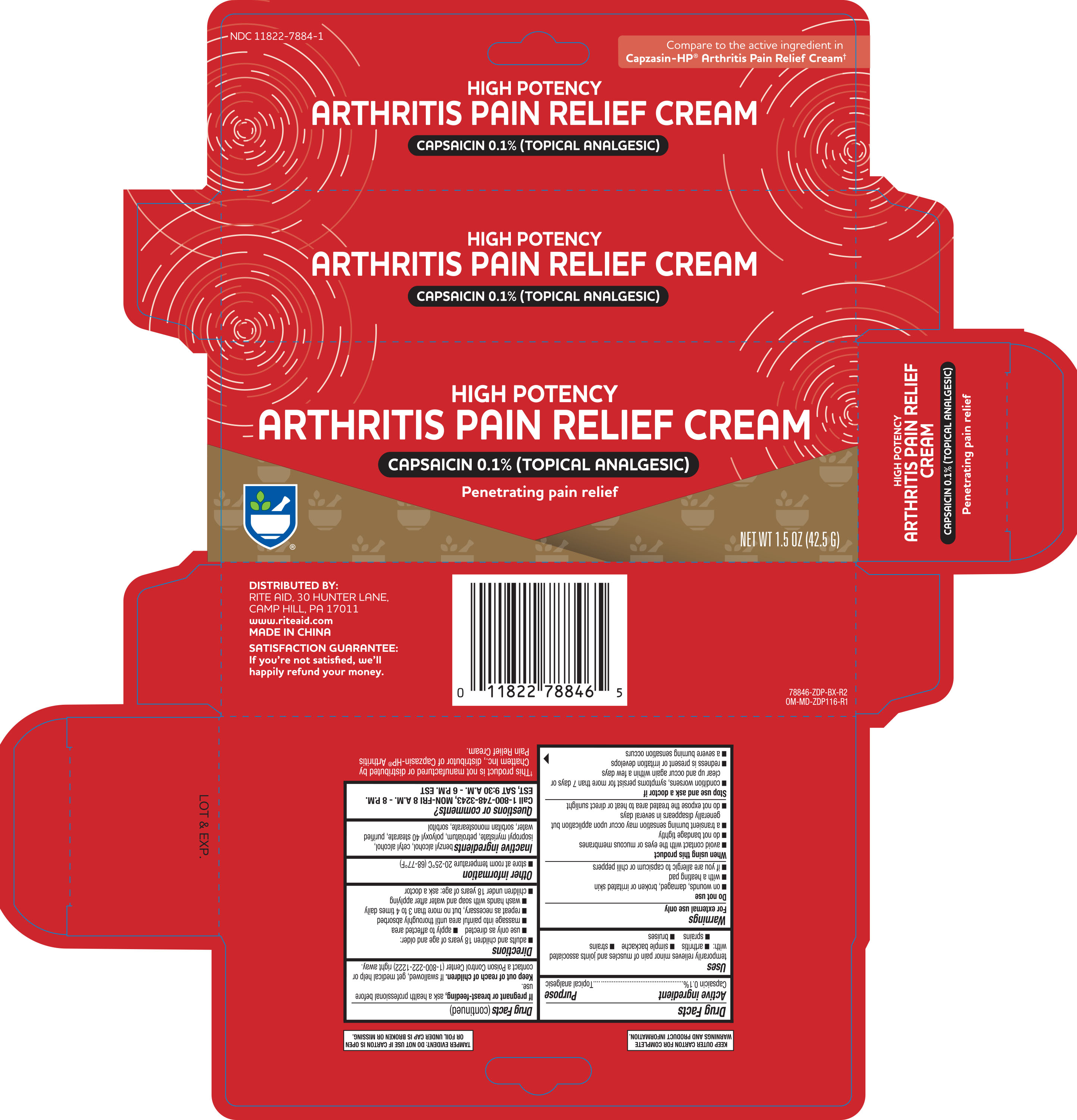 DRUG LABEL: Capsaicin
NDC: 11822-7884 | Form: CREAM
Manufacturer: Rite Aid
Category: otc | Type: HUMAN OTC DRUG LABEL
Date: 20241223

ACTIVE INGREDIENTS: CAPSAICIN 0.001 g/1 g
INACTIVE INGREDIENTS: CETYL ALCOHOL; POLYOXYL 40 STEARATE; WATER; SORBITOL; PETROLATUM; SORBITAN MONOSTEARATE; ISOPROPYL MYRISTATE; BENZYL ALCOHOL

Rite-Aid High Potency Arthritis Pain Relief Cream 1.5 oz ZDP 78846

Active ingredient Purpose

Capsaicin 0.1%....................................................Topical analgesic

Uses

- temporarily relieves minor pain of muscles and joints associated with:
- arthritis
- simple backache
- strains
- sprains
- bruises

Warnings

For external use only

Do not use

- on wounds, damaged, broken or irritated skin
- with a heating pad
- if you are allergic to capsicum or chili peppers

When using this product

- avoid contact with the eyes or mucous membranes
- do not bandage tightly
- a transient burning sensation may occur upon application but generally disappears in several days
- do not expose the treated area to heat or direct sunlight

Stop use and ask a doctor if

- condition worsens, symptoms persist for more than 7 days or clear up and occur again within a few days
- redness is present or irriration develops
- a severe burning sensation occurs

PREGNANCY OR BREAST FEEDING

If pregnant or breast-feeding, ask a health professional before use.

Keep out of reach of children. If swallowed, get medical help or contact a Poison Control Center (1-800-222-1222) right away.

Directions

- adults and children 18 years of age and older:
- use only as directed
- apply to affected area
- massage into painful area until thoroughly absorbed
- repeat as necessary, but no more than 3 to 4 times daily
- wash hands with soap and water after applying
- children under 18 years of age: ask a doctor

Other information

- store at room temperature 20-25°C (68-77°F)

INACTIVE INGREDIENT

Inactivate ingredients

benzyl alcohol, cetyl alcohol, isopropyl myristate, petrolatum, polyoxyl 40 stearate, purified water, sorbitan monostearate, sorbital

DOSAGE AND ADMINISTRATION

Distributed by:

Rite Aid

30 Hunter Lane

Camp Hill, PA 17011

Made in China